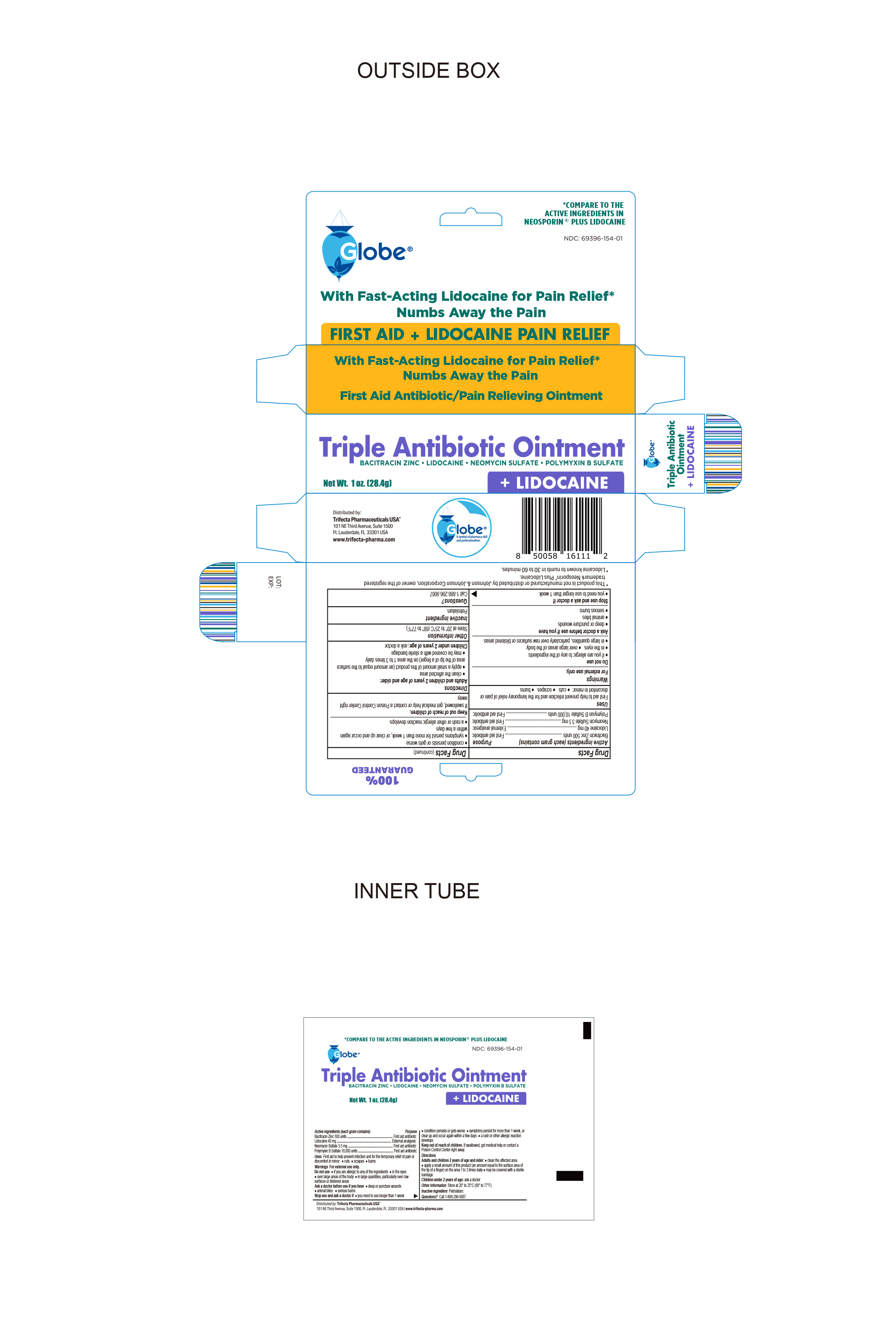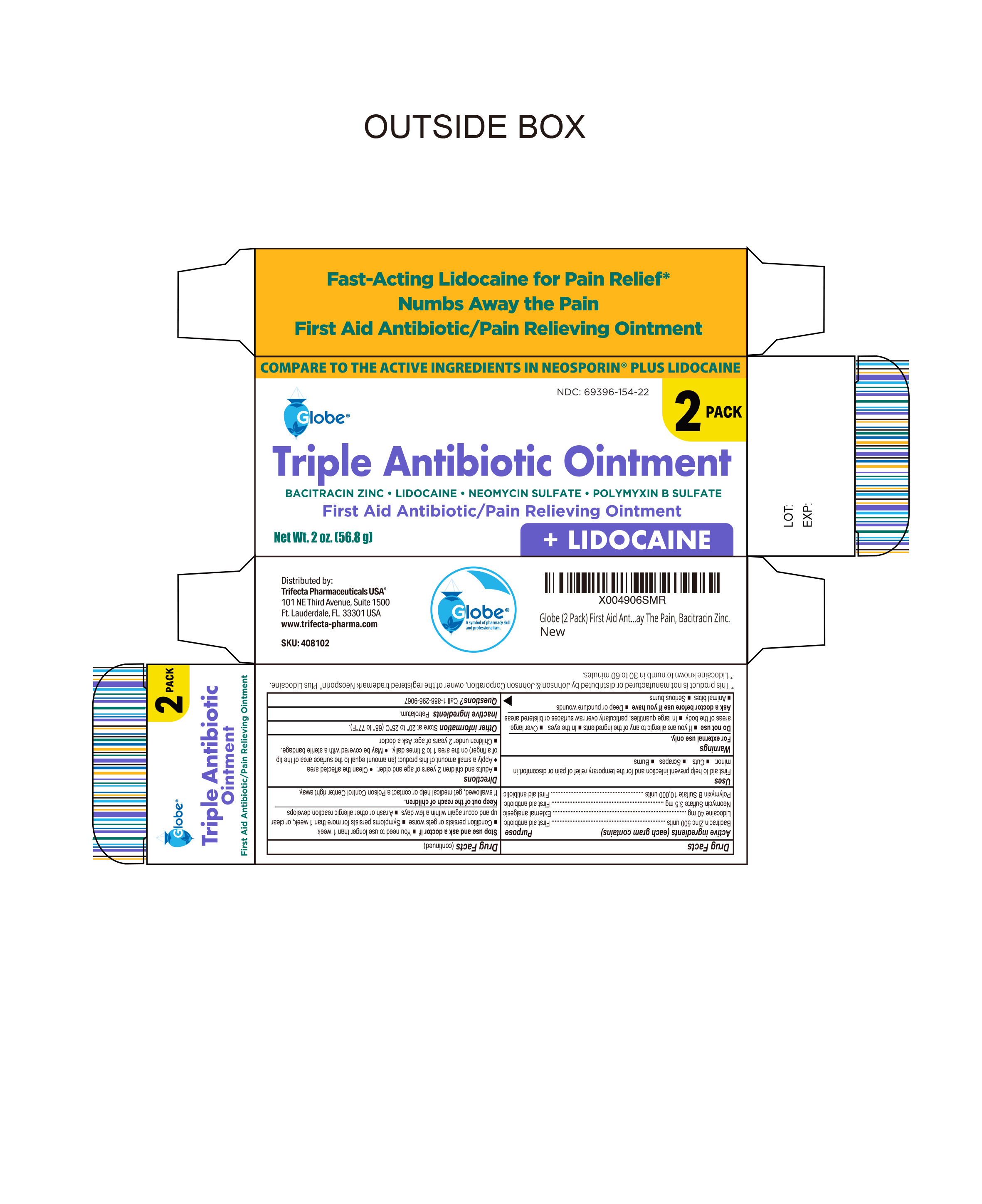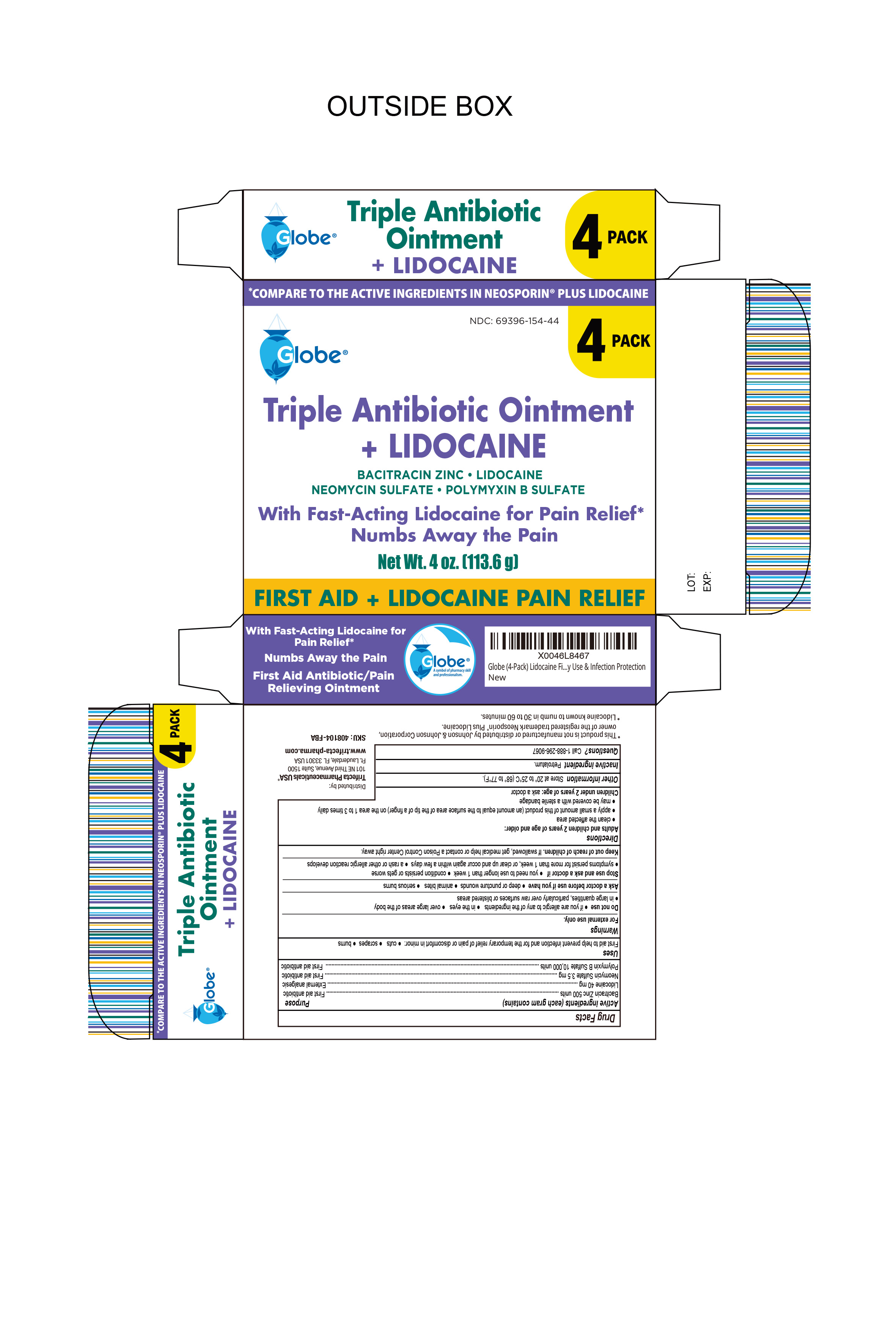 DRUG LABEL: Triple Antibiotic plus Lidocaine
NDC: 69396-154 | Form: OINTMENT
Manufacturer: TRIFECTA PHARMACEUTICALS USA LLC
Category: otc | Type: HUMAN OTC DRUG LABEL
Date: 20250424

ACTIVE INGREDIENTS: BACITRACIN ZINC 500 [USP'U]/1 g; NEOMYCIN SULFATE 3.5 mg/1 g; POLYMYXIN B SULFATE 10000 [USP'U]/1 g; LIDOCAINE 40 mg/1 g
INACTIVE INGREDIENTS: PETROLATUM

Triple Antibiotic Ointment + Lidocaine

Active ingredients (each gram contains)

Bacitracin zinc 500 units
Neomycin sulfate 3.5 mg
Polymyxin B sulfate 10,000 units

Purpose

First aid antibiotic

Active Ingredient

Lidocaine 40mg

Purpose

External Analgesic

Uses

Uses first aid to help prevent infection and for the temporary relief of pain or discomfort in minor:● cuts ● scrapes ● burns

Keep out of reach of children. If swallowed, get medical help or contact a Poison Control Center right away.

Warnings

For external use only.

Ask Doctor Before use if you have

- Deep or puncture wounds
- Animal bites
- serious burns

Do Not Use

- If you are allergic to any of the ingredients
- In the eyes
- Over large areas of the body
- In large quantities, particularly over raw surfaces or blistered areas

Stop Use and Ask a doctor if

- You need to use longer than 1 week
- Condition persists or gets worse
- Symptoms persist for more than 1 week or clear up and occur again within a few days
- Rash or other allergic reaction develops

Directions

- Adults and Children 2 years of age and older
- Clean the affected area
- Apply a small amount of this product (an amount equal to the surface area of the tip of a finger) on the area 1 to 3 times daily
- May be covered with a sterile bandage
- Children under 2 years of age, Ask a doctor

Questions

Questions? Call 1-888-296-9067

Inactive Ingredient

Petrolatum

Other information

● store at 20° to 25°C (68° to 77°F)

Distributed By

Trifecta Pharmaceuticals USA®
101 NE Third Avenue, Suite 1500
Ft. Lauderdale, FL 33301, USA
1-888-296-9067

* This product is not manufactured or distributed by Johnson & Johnson Corporation, owner of the registered trademark Neosporin® plus Lidocaine

Lidocaine known to numb in 30 to 60 minutes.